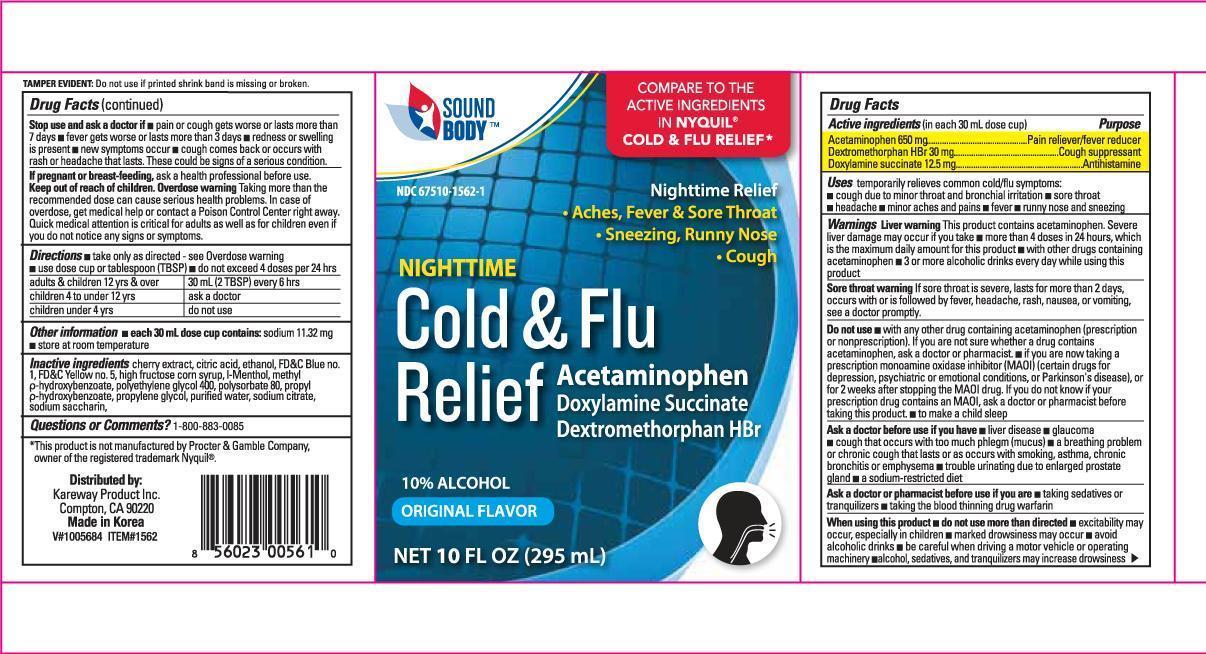 DRUG LABEL: Night Time Cold/Flu Relief Original
NDC: 67510-1562 | Form: LIQUID
Manufacturer: Kareway Product, Inc.
Category: otc | Type: HUMAN OTC DRUG LABEL
Date: 20131212

ACTIVE INGREDIENTS: ACETAMINOPHEN 650 mg/30 mL; DEXTROMETHORPHAN HYDROBROMIDE 30 mg/30 mL; DOXYLAMINE SUCCINATE 12.5 mg/30 mL
INACTIVE INGREDIENTS: CITRIC ACID MONOHYDRATE; FD&C BLUE NO. 1; FD&C YELLOW NO. 5; HIGH FRUCTOSE CORN SYRUP; POLYETHYLENE GLYCOL 400; POLYSORBATE 80; PROPYLENE GLYCOL; WATER; SODIUM CITRATE; SACCHARIN SODIUM DIHYDRATE

Drug Facts

Active ingredients (in each 30mL dose cup)

Acetaminophen 650 mg

Dextromethorphan HBr 30 mg

Doxylamine succinate 12.5 mg

Purpose

Pain reliever/fever reducer

Cough suppressant

Antihistamine

Uses

- temporarily relieves common cold/flu symptoms:
- cough due to minor throat and bronchial irritation
- sore throat
- headache
- minor aches and pains
- fever
- runny nose and sneezing

Warnings

Liver warning

- This product contains acetaminophen. Severe liver damage may occur if you take
- more than 4 doses in 24 hours, which is the maximum daily amount for this product
- with other drugs containing acetaminophen
- 3 or more alcoholic drinks every day while using this product

Sore throat warning:

- If sore throat is severe, persists for more than 2 days, occurs with or is followed by fever, headache, rash, nausea, or vomiting, see a doctor promptly.

Do not use

- with any other drug containing acetaminophen (prescription or nonprescription). If you are not sure whether a drug contains acetaminophen, ask a doctor or pharmacist.
- if you are now taking a prescription monoamine oxidase inhibitor (MAOI) (certain drugs for depression, psychiatric, or emotional conditions, or Parkinson's disease), or for 2 weeks after stopping the MAOI drug. If you do not know if your prescription drug contains an MAOI, ask a doctor or pharmacist before taking this product.
- to make a child sleep

Ask a doctor before use if you have

- liver disease
- glaucoma
- cough that occurs with too much phlegm (mucus)
- a breathing problem or chronic cough that lasts or as occurs with smoking, asthma, chronic bronchitis or emphysema
- trouble urinating due to enlarged prostate gland
- a sodium-restricted diet

Ask a doctor or pharmacist before use if you are

- taking sedatives or tranquilizers.
- taking the blood thinning drug warfarin

When using this product

- do not use more than directed
- excitability may occur, especially in children.
- marked drowsiness may occur
- avoid alcoholic drinks
- be careful when driving a motor vehicle or operating machinery
- alcohol, sedatives, and tranquilizers may increase drowsiness

Stop use and ask a doctor if

- pain or cough gets worse or lasts more than 7 days
- fever gets worse or lasts more than 3 days
- redness or swelling is present
- new symptoms occur
- cough comes back or occurs with rash or headache that lasts.
- These could be signs of a serious condition.

If pregnant or breast-feeding,

- ask a health professional before use.

Overdose warning

- Taking more than the recommended dose can cause serious health problems. In case of overdose, get medical help or contact a Poison Control Center right away. Quick medical attention is critical for adults as well as for children even if you do not notice any signs or symptoms.

Directions

- take only as directed - see Overdose warning
- use dose cup or tablespoon (TBSP)
- do not exceed 4 doses per 24 hours

adults and children 12 yrs and over | 30 ml (2 Tbsp) every 6 hours
children 4 to under 12 yrs | ask a doctor
children under 4 yrs | do not use

Other information

- each 30 mL dose cup contains: sodium 11.32 mg
- store at room temperature

Inactive ingredients

cherry extract, citric acid, ethanol, FD and C blue no.1, FD and C yellow no.5, high fructose corn syrup, I-menthol, methyl p-hydroxybenzoate, polyethylene glycol 400, polysorbate 80, propyl p-hydroxybenzoate, propylene glycol, purified water, sodium citrate, sodium saccharin

Questions or Comments?

1-800-883-0085

Package Label

Nighttime Cold and Flu